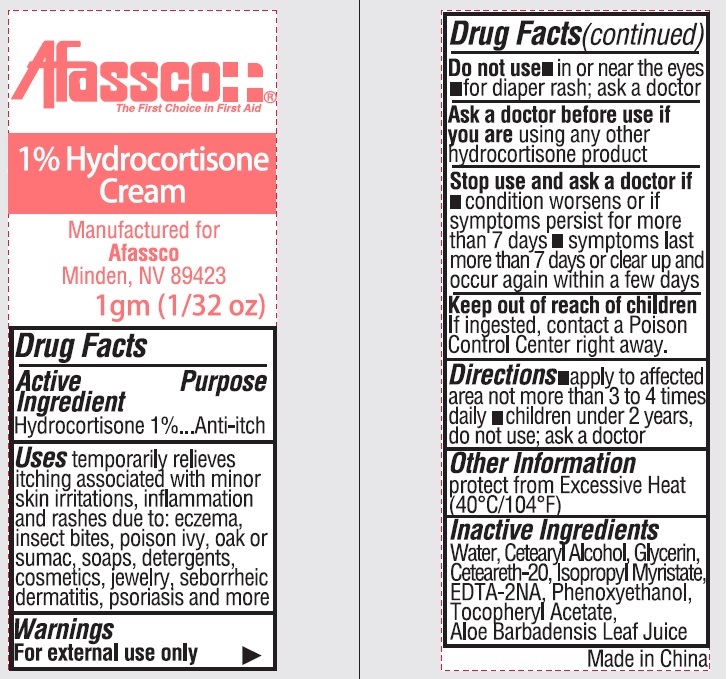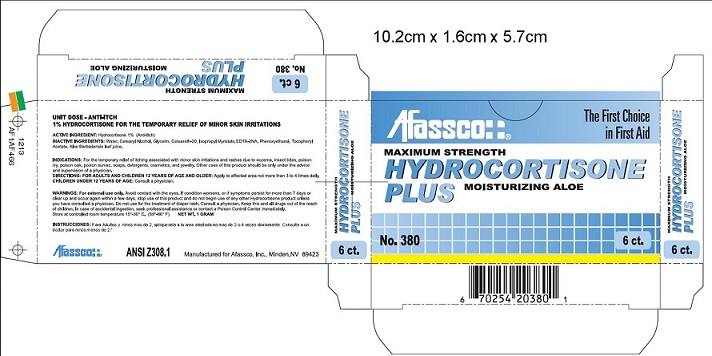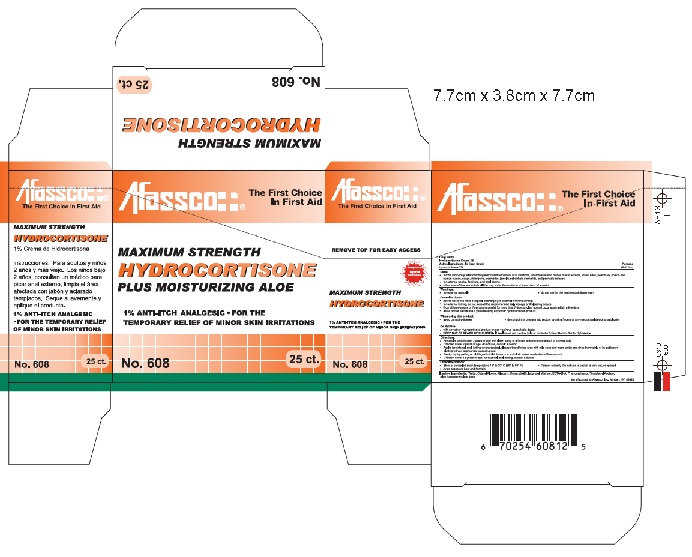 DRUG LABEL: AFASSCO 1% Hydrocortisone
NDC: 51532-4608 | Form: OINTMENT
Manufacturer: Afassco Inc.
Category: otc | Type: HUMAN OTC DRUG LABEL
Date: 20230112

ACTIVE INGREDIENTS: HYDROCORTISONE 0.01 g/1 g
INACTIVE INGREDIENTS: WATER; CETOSTEARYL ALCOHOL; GLYCERIN; POLYOXYL 20 CETOSTEARYL ETHER; ISOPROPYL MYRISTATE; EDETATE DISODIUM; PHENOXYETHANOL; .ALPHA.-TOCOPHEROL ACETATE, D-; ALOE VERA LEAF

1% Hydrocortisone Cream

Drug Facts

Hydrocorticone Cream 1%

Active Ingredients (In Each Gram)

Hydrocortisone 1%

Purpose

Anti-itch

Uses:

- for the temporary temporarily relief of itching associated with minor skin irritations, inflammation and rashes due to eczema, insect bites, poison ivy, poison oak, poison sumac, soaps, detergents, cosmetics, jewelry, seborrheic dermatitis, and psoriasis scrapes
- for external genital, feminine, and anal itching
- other uses of this product should be only under the advice and supervision of a doctor

Warnings

- for external use only

Consult a doctor:

- before use if you have a vaginal discharge (for external feminine itching)
- for external itching, do not exceed the recommended daily dosage or if bleeding occurs
- if condition worsens or if symptoms persist for more than 7 days or clear up and occur again in a few days
- ask a doctor before use if you are using any other hydrocortisone product

When using this product:

- avoid contacty with eyes
- do not put this produce into rectum by using fingers or any mechanical device or applicator

Do not use:

- with any other Hydrocortisone product unless you have consulted a doctor

- KEEP OUT OF REACH OF CHILDREN. If swallowed contact a Poison Control center right away.

Directions

• For adults and children 2 years of age and older; apply to affected area not more than 3 to 4 times daily
• Children under 2 years of age; do not use, consult a doctor
• Adults for external anal itching when practical, cleanse the area with mild soap and warm water and rinse thoroughly or by patting or blotting with an appropriate cleansing pad
• Gently dry by patting or blotting with toilet tissue or soft cloth before application of this product
• Children under 12 years of age; for external itching, consult a doctor

Other Information:

- Store at controlled room temperature 15° to 30° C (59° to 86° F)
- Tamper evident. Do not use if packet is torn, cut, or opened.
- Avoid excessive heat and humidity

Inactive Ingredients

Water, Cetearyl Alcohol, Glycerin,

Ceteareth-20, Isopropyl Myristate,

EDTA-2NA, Phenoxyethanol,

Tocopheryl Acetate,

Aloe Barbadensis Leaf Juice

Principal Display Panel

Afassco¦ ¦®

The First Choice
in First Aid

MAXIMUM STRENGTH
HYDROCORTISONE
PLUS MOISTURIZING ALOE

1% ANTI-ITCH ANALGESIC • FOR THE

TEMPORARY RELIEF OF MINOR SKIN IRRITATIONS

No. 608 25 ct.

Afassco¦ ¦®

The First Choice in First Aid

REMOVE TOP FOR EASY ACCESS

Compare To

Hydrocortisone

MAXIMUM STRENGTH
HYDROCORTISONE

1% ANTI-ITCH ANALGESIC • FOR THE

TEMPORARY RELIEF OF MINOR SKIN IRRITATIONS

No. 608 25 ct.

Afassco¦ ¦®

The First Choice in First Aid

MAXIMUM STRENGTH
HYDROCORTISONE

1% Crema de Fydrocortisona

instructiones: Para Adultos y ninos

2 anos y mas viejo. Los ninos bajo

2 anos, consultan un medico para

picar anal externo. Limpia el areaa

afectada con jabon y aclarado

aplique el producto.

1% ANTI-ITCH ANALGESIC • FOR THE

TEMPORARY RELIEF OF MINOR SKIN IRRITATIONS

No. 608 25 ct.

Afassco¦ ¦®

The First Choice in First Aid

Manufactured for Afassco, Inc. Minden, NV 89423

6 70254 60812 5

↓25 ct. Box↓

↓6 ct. Box↓

↓Unit Dose Package Label↓

Afassco¦ ¦®

The First Choice in First Aid

1% Hydrocortisone

Cream

Manufactured for Afassco

Minden, NV 89423

1gm (1/32 oz)

Made in China

res